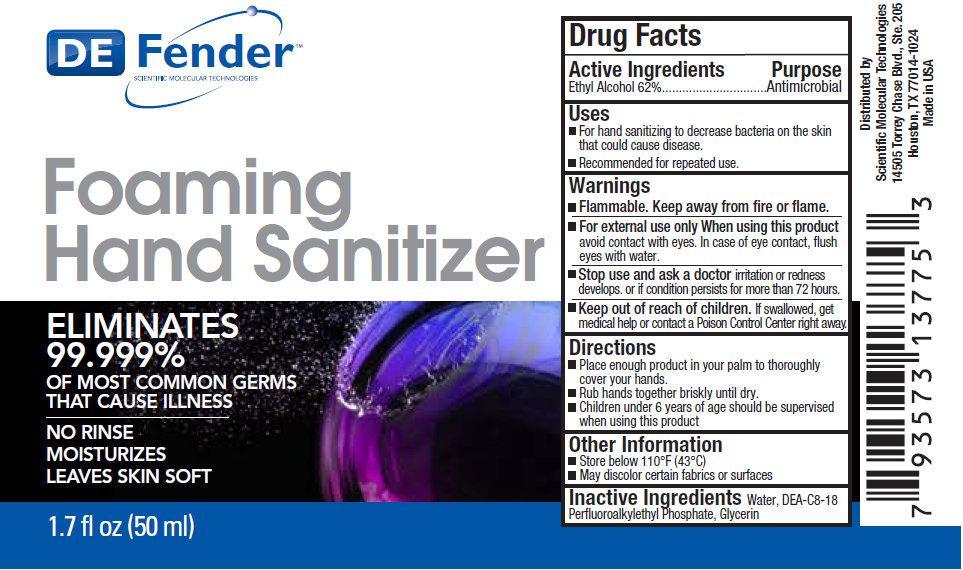 DRUG LABEL: DEFENDER Foaming Hand Sanitizer
NDC: 42953-001 | Form: LIQUID
Manufacturer: Scientific Molecular Technologies
Category: otc | Type: HUMAN OTC DRUG LABEL
Date: 20210601

ACTIVE INGREDIENTS: ALCOHOL 62 mL/100 mL
INACTIVE INGREDIENTS: WATER; DIETHANOLAMINE BIS(C8-C18 PERFLUOROALKYLETHYL)PHOSPHATE; GLYCERIN

DEFENDER Foaming Hand Sanitizer

Active Ingredients

Ethyl Alcohol 62%

Purpose

Antimicrobial

Uses

- For hand sanitizing to decrease bacteria on the skin that could cause disease.
- Recommended for repeated use.

Warnings

- Flammable. Keep away from fire or flame.
- For external use only

When using this product

avoid contact with eyes. In case of eye contact, flush eyes with water.

Stop use and ask a doctor

if irritation or redness develops or if condition persists for more than 72 hours.

Keep out of reach of children.

If swallowed, get medical help or contact a Poison Control Center right away.

Directions

- Place enough product in your palm to thoroughly cover your hands.
- Rub hands together briskly until dry.
- Children under 6 years of age should be supervised when using this product

Other Information

- Store below 110^0F (43^0C)
- May discolor certain fabrics or surfaces

Inactive Ingredients

Water, DEA-C8-18 Perfluoroalkylethyl Phosphate, Glycerin

PACKAGE LABEL

DE Fender SCIENTIFIC MOLECULAR TECHNOLOGIES Foaming Hand Sanitizer ELIMINATES 99.999% OF MOST COMMON GERMS THAT CAUSE ILLNESS NO RINSE MOISTURIZES LEAVES SKIN SOFT 1.7 fl oz (50 ml)